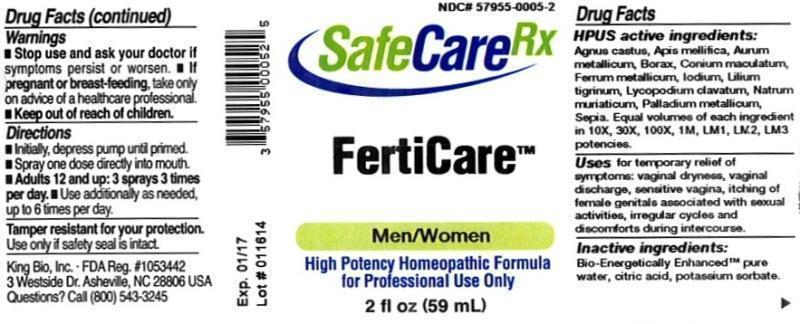 DRUG LABEL: FertiCare
NDC: 57955-0005 | Form: LIQUID
Manufacturer: King Bio Inc.
Category: homeopathic | Type: HUMAN OTC DRUG LABEL
Date: 20140417

ACTIVE INGREDIENTS: CHASTE TREE 10 [hp_X]/59 mL; APIS MELLIFERA 10 [hp_X]/59 mL; GOLD 10 [hp_X]/59 mL; SODIUM BORATE 10 [hp_X]/59 mL; CONIUM MACULATUM FLOWERING TOP 10 [hp_X]/59 mL; IRON 10 [hp_X]/59 mL; IODINE 10 [hp_X]/59 mL; LILIUM LANCIFOLIUM WHOLE FLOWERING 10 [hp_X]/59 mL; LYCOPODIUM CLAVATUM SPORE 10 [hp_X]/59 mL; SODIUM CHLORIDE 10 [hp_X]/59 mL; PALLADIUM 10 [hp_X]/59 mL; SEPIA OFFICINALIS JUICE 10 [hp_X]/59 mL
INACTIVE INGREDIENTS: WATER; CITRIC ACID MONOHYDRATE; POTASSIUM SORBATE

FertiCare™

ACTIVE INGREDIENT

Drug Facts__________________________________________________________________________________________________________

HPUS active ingredients: Agnus castus, Apis mellifica, aurum metallicum, Borax, Conium maculatum, Ferrum metallicum, Iodium, Lilium tigrinum, Lycopodium clavatum, Natrum muriatcum, Palladium metallicum, sepia. Equal volumes of each ingredient in 10X, 30X, 100X, 1M, LM1, LM2, LM3 potencies.

INDICATIONS AND USAGE

Uses for temporary relief of symptoms: vaginal dryness, vaginal discharge, sensitive vagina, itching of female genitals associated with sexual activities, irregular cycles and discomforts during intercourse.

Inactive Ingredients:

Bio-Energetically Enhanced™ pure water, citric acid and potassium sorbate.

Warnings

- Stop use and ask your doctor if symptoms persist or worsen.
- If pregnant or breast-feeding, take only on advice of a healthcare professional.

- Keep out of reach of children

Directions

- Initially, depress pump until primed.
- Spray one dose directly into mouth.
- Adults 12 and up: 3 sprays 3 times per day.
- Use additionally as needed, up to 6 times per day.

OTHER SAFETY INFORMATION

Tamper resistant for your protection. Use only if safety seal is intact.

PURPOSE

Uses for temporary relief of symptoms:

- vaginal dryness
- vaginal discharge
- sensitive vagina
- itching of female genitals associated with sexual activities
- irregular cycles
- discomforts during intercourse